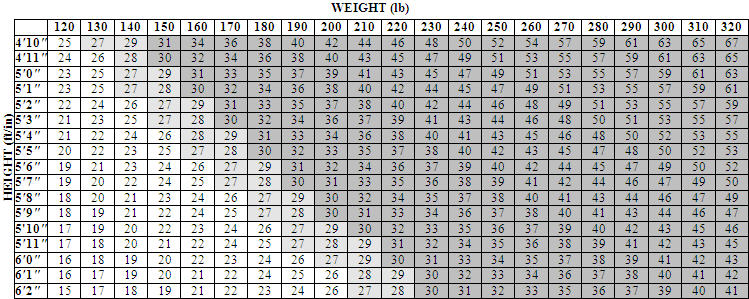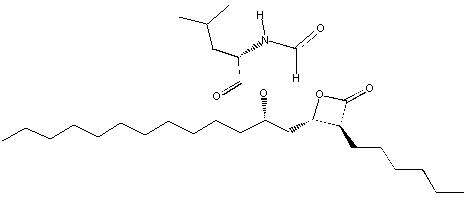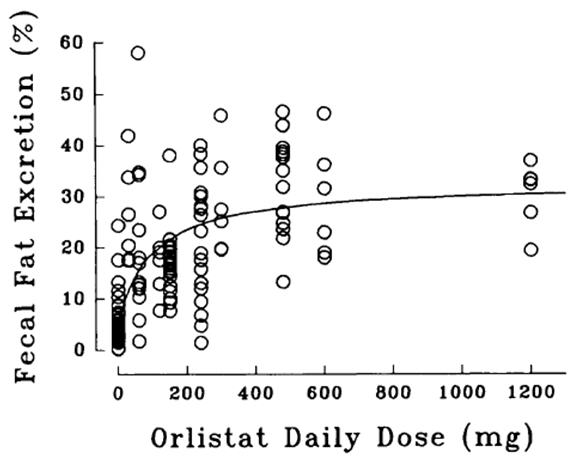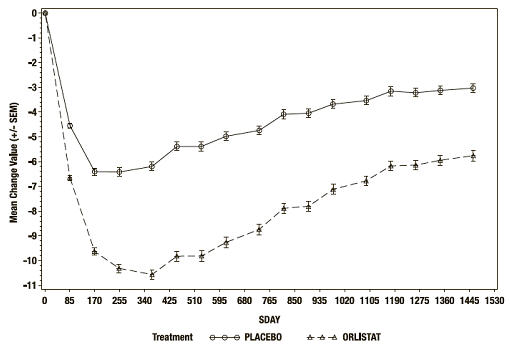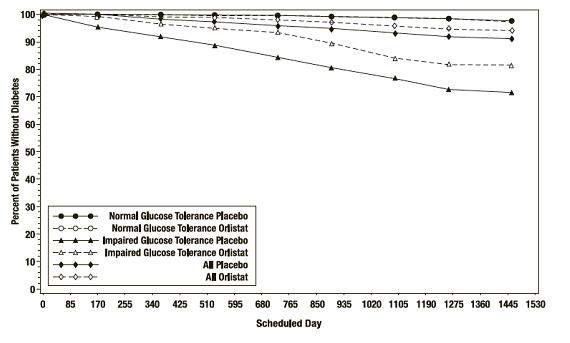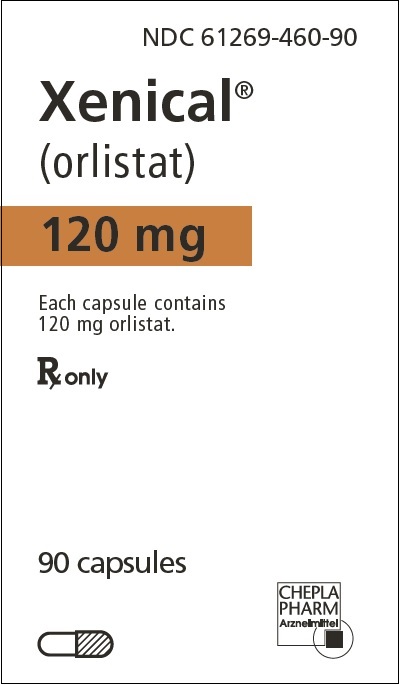 DRUG LABEL: Xenical
NDC: 61269-460 | Form: CAPSULE
Manufacturer: H2-Pharma LLC
Category: prescription | Type: HUMAN PRESCRIPTION DRUG LABEL
Date: 20240708

ACTIVE INGREDIENTS: ORLISTAT 120 mg/1 1
INACTIVE INGREDIENTS: MICROCRYSTALLINE CELLULOSE; SODIUM STARCH GLYCOLATE TYPE A POTATO; SODIUM LAURYL SULFATE; POVIDONE, UNSPECIFIED; TALC; GELATIN, UNSPECIFIED; TITANIUM DIOXIDE; FD&C BLUE NO. 2; SHELLAC; PROPYLENE GLYCOL; AMMONIA; POTASSIUM HYDROXIDE; FERROSOFERRIC OXIDE

HIGHLIGHTS OF PRESCRIBING INFORMATION

These highlights do not include all the information needed to use XENICAL safely and effectively.
See full prescribing information for XENICAL.
XENICAL (orlistat) Capsules for oral use
Initial U.S. Approval: 1999

RECENT MAJOR CHANGES

- Warnings and Precautions, Oxalate Nephrolithiasis and Oxalate Nephropathy with Renal Failure (5.3) 11/2022

1 INDICATIONS AND USAGE

- XENICAL is a reversible inhibitor of gastrointestinal lipases indicated for obesity management including weight loss and weight maintenance when used in conjunction with a reduced-calorie diet. (1)
- XENICAL is also indicated to reduce the risk for weight regain after prior weight loss. (1)

2 DOSAGE AND ADMINISTRATION

- One 120-mg capsule three times a day with each main meal containing fat (during or up to 1 hour after the meal). (2)
- Advise patients to take a nutritionally balanced, reduced-calorie diet that contains approximately 30% of calories from fat. (2)
- Distribute the daily intake of fat, carbohydrate, and protein over three main meals. (2)
- Advise patients to take a multivitamin containing fat-soluble vitamins to ensure adequate nutrition. (2)
- Take the vitamin supplement at least 2 hours before or after the administration of XENICAL, such as at bedtime. (2)
- For patients receiving both XENICAL and cyclosporine therapy, administer cyclosporine 3 hours after XENICAL. (2)
- For patients receiving both XENICAL and levothyroxine therapy, administer levothyroxine and XENICAL at least 4 hours apart. (2)

3 DOSAGE FORMS AND STRENGTHS

- Capsules: 120 mg. (3)

4 CONTRAINDICATIONS

- Pregnancy (4, 8.1)
- Chronic malabsorption syndrome (4)
- Cholestasis (4)
- Known hypersensitivity to XENICAL or to any component of this product (4)

5 WARNINGS AND PRECAUTIONS

- XENICAL has drug interactions and can decrease vitamin absorption. (5.1, 7)
- Take a multivitamin supplement that contains fat-soluble vitamins to ensure adequate nutrition. (5.1)
- Rare cases of severe liver injury with hepatocellular necrosis or acute hepatic failure have been reported. (5.2)
- Patients may develop oxalate nephrolithiasis and oxalate nephropathy following treatment with XENICAL. Monitor renal function in patients at risk for renal insufficiency. Discontinue XENICAL if oxalate nephropathy develops. (5.3)
- Substantial weight loss can increase the risk of cholelithiasis. (5.4)
- Exclude organic causes of obesity (eg, hypothyroidism) before prescribing XENICAL. (5.5)
- Gastrointestinal events may increase when XENICAL is taken with a diet high in fat (>30% total daily calories from fat). (5.5)

6 ADVERSE REACTIONS

Most common treatment emergent adverse reactions (≥5% and at least twice that of placebo) include oily spotting, flatus with discharge, fecal urgency, fatty/oily stool, oily evacuation, increased defecation and fecal incontinence. (6.1)

To report SUSPECTED ADVERSE REACTIONS, contact the Safety Call Center at 1-888-236-5445 or FDA at 1‑800‑FDA‑1088 (1-800-332-1088) or www.fda.gov/medwatch.

7 DRUG INTERACTIONS

- Cyclosporine: Reduction in cyclosporine plasma levels was observed when XENICAL was coadministered with cyclosporine. (7.1)
- Fat-soluble Vitamin Supplements and Analogues: All patients should take a daily multivitamin that contains vitamins A, D, E, K, and beta-carotene. (7.2)
- Levothyroxine: Patients treated concomitantly with XENICAL and levothyroxine should be monitored for changes in thyroid function. (7.3)
- Warfarin: Patients on chronic stable doses of warfarin who are prescribed XENICAL should be monitored closely for changes in coagulation parameters. (7.4)
- Amiodarone: A reduction in exposure to amiodarone was observed when XENICAL was co-administered. (7.5)
- Antiepileptic Drugs: Convulsions have been reported in patients taking XENICAL with antiepileptic drugs. Patients should be monitored for possible changes in frequency or severity of convulsions. (7.6)
- Antiretroviral Drugs: Loss of virological control has been reported in HIV-infected patients. Patients should be monitored frequently for changes in HIV RNA levels. (7.7)

8 USE IN SPECIFIC POPULATIONS

- Nursing Mothers: Caution should be exercised when administered to a nursing woman. (8.3)

FULL PRESCRIBING INFORMATION

1 INDICATIONS AND USAGE

XENICAL is indicated for obesity management including weight loss and weight maintenance when used in conjunction with a reduced-calorie diet. XENICAL is also indicated to reduce the risk for weight regain after prior weight loss. XENICAL is indicated for obese patients with an initial body mass index (BMI) ≥30 kg/m^2 or ≥27 kg/m^2 in the presence of other risk factors (e.g., hypertension, diabetes, dyslipidemia).

Table 1 illustrates body mass index (BMI) according to a variety of weights and heights. The BMI is calculated by dividing weight in kilograms by height in meters squared. For example, a person who weighs 180 lbs and is 5 '5 " would have a BMI of 30.

Table 1 Body Mass Index (BMI), kg/m^2 [Conversion Factors: Weight in lbs ÷ 2.2 = weight in kilograms (kg) Height in inches × 0.0254 = height in meters (m) 1 foot = 12 inches]

2 DOSAGE AND ADMINISTRATION

2.1 Recommended Dosing

The recommended dose of XENICAL is one 120-mg capsule three times a day with each main meal containing fat (during or up to 1 hour after the meal).

The patient should be on a nutritionally balanced, reduced-calorie diet that contains approximately 30% of calories from fat. The daily intake of fat, carbohydrate, and protein should be distributed over three main meals. If a meal is occasionally missed or contains no fat, the dose of XENICAL can be omitted.

Because XENICAL has been shown to reduce the absorption of some fat-soluble vitamins and beta-carotene, patients should be counseled to take a multivitamin containing fat-soluble vitamins to ensure adequate nutrition [see Warnings and Precautions (5.1)] . The vitamin supplement should be taken at least 2 hours before or after the administration of XENICAL, such as at bedtime.

For patients receiving both XENICAL and cyclosporine therapy, administer cyclosporine 3 hours after XENICAL.

For patients receiving both XENICAL and levothyroxine therapy, administer levothyroxine and XENICAL at least 4 hours apart. Patients treated concomitantly with XENICAL and levothyroxine should be monitored for changes in thyroid function.

Doses above 120 mg three times a day have not been shown to provide additional benefit.

Based on fecal fat measurements, the effect of XENICAL is seen as soon as 24 to 48 hours after dosing. Upon discontinuation of therapy, fecal fat content usually returns to pretreatment levels within 48 to 72 hours.

3 DOSAGE FORMS AND STRENGTHS

XENICAL 120 mg turquoise capsules imprinted with XENICAL 120 in black ink.

4 CONTRAINDICATIONS

XENICAL is contraindicated in:

- Pregnancy [see Use in Specific Populations (8.1)]
- Patients with chronic malabsorption syndrome
- Patients with cholestasis
- Patients with known hypersensitivity to XENICAL or to any component of this product

5 WARNINGS AND PRECAUTIONS

5.1 Drug Interactions and Decreased Vitamin Absorption

XENICAL may interact with concomitant drugs including cyclosporine, levothyroxine, warfarin, amiodarone, antiepileptic drugs, and antiretroviral drugs [see Drug Interactions (7)].

Data from a XENICAL and cyclosporine drug interaction study indicate a reduction in cyclosporine plasma levels when XENICAL was coadministered with cyclosporine. Therefore, XENICAL and cyclosporine should not be simultaneously coadministered. To reduce the chance of a drug-drug interaction, cyclosporine should be taken at least 3 hours before or after XENICAL in patients taking both drugs. In addition, in those patients whose cyclosporine levels are being measured, more frequent monitoring should be considered.

Patients should be strongly encouraged to take a multivitamin supplement that contains fat-soluble vitamins to ensure adequate nutrition because XENICAL has been shown to reduce the absorption of some fat-soluble vitamins and beta-carotene [see Dosage and Administration (2), and Adverse Reactions (6.1)] . In addition, the levels of vitamin D and beta-carotene may be low in obese patients compared with non-obese subjects. The supplement should be taken once a day at least 2 hours before or after the administration of XENICAL, such as at bedtime.

Weight-loss may affect glycemic control in patients with diabetes mellitus. A reduction in dose of oral hypoglycemic medication (e.g., sulfonylureas) or insulin may be required in some patients [see Clinical Studies (14)] .

5.2 Liver Injury

There have been rare postmarketing reports of severe liver injury with hepatocellular necrosis or acute hepatic failure in patients treated with XENICAL, with some of these cases resulting in liver transplant or death. Patients should be instructed to report any symptoms of hepatic dysfunction (anorexia, pruritus, jaundice, dark urine, light-colored stools, or right upper quadrant pain) while taking XENICAL. When these symptoms occur, XENICAL and other suspect medications should be discontinued immediately and liver function tests and ALT and AST levels obtained.

5.3 Oxalate Nephrolithiasis and Oxalate Nephropathy with Renal Failure

Some patients may develop increased levels of urinary oxalate following treatment with XENICAL. Cases of oxalate nephrolithiasis and oxalate nephropathy with renal failure have been reported. Monitor renal function when prescribing XENICAL to patients at increased risk for oxalate nephropathy, including patients with renal impairment and in those with a history of hyperoxaluria or calcium oxalate nephrolithiasis. Discontinue XENICAL in patients who develop oxalate nephropathy.

5.4 Cholelithiasis

Substantial weight loss can increase the risk of cholelithiasis. In a clinical trial of XENICAL for the prevention of type 2 diabetes, the rates of cholelithiasis as an adverse event were 2.9% (47/1649) for patients randomized to XENICAL and 1.8% (30/1655) for patients randomized to placebo.

5.5 Miscellaneous

Organic causes of obesity (e.g., hypothyroidism) should be excluded before prescribing XENICAL.

Patients should be advised to adhere to dietary guidelines [see Dosage and Administration (2)] . Gastrointestinal events [see Adverse Reactions (6.1)] may increase when XENICAL is taken with a diet high in fat (>30% total daily calories from fat). The daily intake of fat should be distributed over three main meals. If XENICAL is taken with any one meal very high in fat, the possibility of gastrointestinal effects increases.

6 ADVERSE REACTIONS

6.1 Clinical Trials

Because clinical trials are conducted under widely varying conditions, adverse reaction rates observed in the clinical trials of a drug cannot be directly compared to rates in the clinical trials of another drug and may not reflect the rates observed in patients.

Commonly Observed (based on first year and second year data)

Gastrointestinal (GI) symptoms were the most commonly observed treatment-emergent adverse events associated with the use of XENICAL in the seven double-blind, placebo-controlled clinical trials and are primarily a manifestation of the mechanism of action. (Commonly observed is defined as an incidence of ≥5% and an incidence in the XENICAL 120 mg group that is at least twice that of placebo.)

Table 2 Commonly Observed Adverse Events
Adverse Event | Year 1 |  | Year 2
Adverse Event | XENICAL [Treatment designates XENICAL three times a day plus diet or placebo plus diet] % Patients (N=1913) | Placebo % Patients (N=1466) | XENICAL % Patients (N=613) | Placebo % Patients (N=524)
Oily Spotting [Oily discharge may be clear or have a coloration such as orange or brown.] | 26.6 | 1.3 | 4.4 | 0.2
Flatus with Discharge | 23.9 | 1.4 | 2.1 | 0.2
Fecal Urgency | 22.1 | 6.7 | 2.8 | 1.7
Fatty/Oily Stool | 20.0 | 2.9 | 5.5 | 0.6
Oily Evacuation | 11.9 | 0.8 | 2.3 | 0.2
Increased Defecation | 10.8 | 4.1 | 2.6 | 0.8
Fecal Incontinence | 7.7 | 0.9 | 1.8 | 0.2

In general, the first occurrence of these events was within 3 months of starting therapy. Overall, approximately 50% of all episodes of GI adverse events associated with XENICAL treatment lasted for less than 1 week, and a majority lasted for no more than 4 weeks. However, GI adverse events may occur in some individuals over a period of 6 months or longer.

Discontinuation of Treatment

In controlled clinical trials, 8.8% of patients treated with XENICAL discontinued treatment due to adverse events, compared with 5.0% of placebo-treated patients. For XENICAL, the most common adverse events resulting in discontinuation of treatment were gastrointestinal.

Other Adverse Clinical Events

The following table lists other treatment-emergent adverse events from seven multicenter, double-blind, placebo-controlled clinical trials that occurred at a frequency of ≥2% among patients treated with XENICAL 120 mg three times a day and with an incidence that was greater than placebo during year 1 and year 2, regardless of relationship to study medication.

Table 3 Other Treatment-Emergent Adverse Events From Seven Placebo-Controlled Clinical Trials
Body System/Adverse Event | Year 1 |  | Year 2
Body System/Adverse Event | XENICAL [Treatment designates XENICAL 120 mg three times a day plus diet or placebo plus diet] % Patients (N=1913) | Placebo % Patients (N=1466) | XENICAL % Patients (N=613) | Placebo % Patients (N=524)
– None reported at a frequency ≥2% and greater than placebo
Gastrointestinal System
Abdominal Pain/Discomfort | 25.5 | 21.4 | – | –
Nausea | 8.1 | 7.3 | 3.6 | 2.7
Infectious Diarrhea | 5.3 | 4.4 | – | –
Rectal Pain/Discomfort | 5.2 | 4.0 | 3.3 | 1.9
Tooth Disorder | 4.3 | 3.1 | 2.9 | 2.3
Gingival Disorder | 4.1 | 2.9 | 2.0 | 1.5
Vomiting | 3.8 | 3.5 | – | –
Respiratory System
Influenza | 39.7 | 36.2 | – | –
Upper Respiratory Infection | 38.1 | 32.8 | 26.1 | 25.8
Lower Respiratory Infection | 7.8 | 6.6 | – | –
Ear, Nose & Throat Symptoms | 2.0 | 1.6 | – | –
Musculoskeletal System
Back Pain | 13.9 | 12.1 | – | –
Pain Lower Extremities | – | – | 10.8 | 10.3
Arthritis | 5.4 | 4.8 | – | –
Myalgia | 4.2 | 3.3 | – | –
Joint Disorder | 2.3 | 2.2 | – | –
Tendonitis | – | – | 2.0 | 1.9
Central Nervous System
Headache | 30.6 | 27.6 | – | –
Dizziness | 5.2 | 5.0 | – | –
Body as a Whole
Fatigue | 7.2 | 6.4 | 3.1 | 1.7
Sleep Disorder | 3.9 | 3.3 | – | –
Skin & Appendages
Rash | 4.3 | 4.0 | – | –
Dry Skin | 2.1 | 1.4 | – | –
Reproductive, Female
Menstrual Irregularity | 9.8 | 7.5 | – | –
Vaginitis | 3.8 | 3.6 | 2.6 | 1.9
Urinary System
Urinary Tract Infection | 7.5 | 7.3 | 5.9 | 4.8
Psychiatric Disorder
Psychiatric Anxiety | 4.7 | 2.9 | 2.8 | 2.1
Depression | – | – | 3.4 | 2.5
Hearing & Vestibular Disorders
Otitis | 4.3 | 3.4 | 2.9 | 2.5
Cardiovascular Disorders
Pedal Edema | – | – | 2.8 | 1.9

Table 4 illustrates the percentage of adult patients on XENICAL and placebo who developed a low vitamin level on two or more consecutive visits during 1 and 2 years of therapy in studies in which patients were not previously receiving vitamin supplementation.

Table 4 Incidence of Low Vitamin Values on Two or More Consecutive Visits (Nonsupplemented Adult Patients With Normal Baseline Values - First and Second Year)
 | Placebo [Treatment designates placebo plus diet or XENICAL plus diet] | XENICAL
Vitamin A | 1.0% | 2.2%
Vitamin D | 6.6% | 12.0%
Vitamin E | 1.0% | 5.8%
Beta-carotene | 1.7% | 6.1%

Table 5 illustrates the percentage of adolescent patients on XENICAL and placebo who developed a low vitamin level on two or more consecutive visits during the 1-year study.

Table 5 Incidence of Low Vitamin Values on Two or More Consecutive Visits (Pediatric Patients With Normal Baseline Values [All patients were treated with vitamin supplementation throughout the course of the study])
 | Placebo [Treatment designates placebo plus diet or XENICAL plus diet] | XENICAL
Vitamin A | 0.0% | 0.0%
Vitamin D | 0.7% | 1.4%
Vitamin E | 0.0% | 0.0%
Beta-carotene | 0.8% | 1.5%

In the 4-year XENDOS study, the general pattern of adverse events was similar to that reported for the 1- and 2-year studies with the total incidence of gastrointestinal-related adverse events occurring in year 1 decreasing each year over the 4-year period.

In clinical trials in obese diabetic patients, hypoglycemia and abdominal distension were also observed.

Pediatric Patients

In clinical trials with XENICAL in adolescent patients ages 12 to 16 years, the profile of adverse reactions was generally similar to that observed in adults.

6.2 Postmarketing Experience

The following adverse reactions have been identified during postapproval use of XENICAL. Because these reactions are reported voluntarily from a population of uncertain size, it is not always possible to reliably estimate their frequency or establish a causal relationship to XENICAL exposure.

- Rare cases of increase in transaminases and in alkaline phosphatase and hepatitis that may be serious have been reported. There have been reports of hepatic failure observed with the use of XENICAL in postmarketing surveillance, with some of these cases resulting in liver transplant or death [see Warnings and Precautions (5.2)] .
- Rare cases of hypersensitivity have been reported with the use of XENICAL. Signs and symptoms have included pruritus, rash, urticaria, angioedema, bronchospasm and anaphylaxis. Very rare cases of bullous eruption have been reported.
- Rare cases of leukocytoclastic vasculitis have been reported. Clinical signs include palpable purpura, maculopapular lesions, or bullous eruption.
- Acute oxalate nephropathy after treatment with XENICAL has been reported in patients with or at risk for renal disease [see Warnings and Precautions (5.3)] .
- Pancreatitis has been reported with the use of XENICAL in postmarketing surveillance. No causal relationship or physiopathological mechanism between pancreatitis and obesity therapy has been definitively established.
- Lower gastrointestinal bleeding has been reported in patients treated with XENICAL. Most reports are nonserious; severe or persistent cases should be investigated further.

7 DRUG INTERACTIONS

7.1 Cyclosporine

Data from a XENICAL and cyclosporine drug interaction study indicate a reduction in cyclosporine plasma levels when XENICAL was coadministered with cyclosporine. XENICAL and cyclosporine should not be simultaneously coadministered. Cyclosporine should be administered 3 hours after the administration of XENICAL [see Dosage and Administration (2), and Warnings and Precautions (5.1)] .

7.2 Fat-soluble Vitamin Supplements and Analogues

Data from a pharmacokinetic interaction study showed that the absorption of beta-carotene supplement is reduced when concomitantly administered with XENICAL. XENICAL inhibited absorption of a vitamin E acetate supplement. The effect of XENICAL on the absorption of supplemental vitamin D, vitamin A, and nutritionally-derived vitamin K is not known at this time [see Clinical Pharmacology (12.3), and Warnings and Precautions (5.1)] .

7.3 Levothyroxine

Hypothyroidism has been reported in patients treated concomitantly with XENICAL and levothyroxine postmarketing. Patients treated concomitantly with XENICAL and levothyroxine should be monitored for changes in thyroid function. Administer levothyroxine and XENICAL at least 4 hours apart [see Dosage and Administration (2)] .

7.4 Anticoagulants including Warfarin

Vitamin K absorption may be decreased with XENICAL. Reports of decreased prothrombin, increased INR and unbalanced anticoagulant treatment resulting in change of hemostatic parameters have been reported in patients treated concomitantly with XENICAL and anticoagulants. Patients on chronic stable doses of warfarin or other anticoagulants who are prescribed XENICAL should be monitored closely for changes in coagulation parameters [see Clinical Pharmacology (12.3)] .

7.5 Amiodarone

A pharmacokinetic study, where amiodarone was orally administered during orlistat treatment, demonstrated a reduction in exposure to amiodarone and its metabolite, desethylamiodarone [see Clinical Pharmocology (12.3)] . A reduced therapeutic effect of amiodarone is possible. The effect of commencing orlistat treatment in patients on stable amiodarone therapy has not been studied.

7.6 Antiepileptic Drugs

Convulsions have been reported in patients treated concomitantly with orlistat and antiepileptic drugs. Patients should be monitored for possible changes in the frequency and/or severity of convulsions.

7.7 Antiretroviral Drugs

Loss of virological control has been reported in HIV-infected patients taking orlistat concomitantly with antiretroviral drugs such as atazanavir, ritonavir, tenofovir disoproxil fumarate, emtricitabine, and with the combinations lopinavir/ritonavir and emtricitabine/efavirenz/tenofovir disoproxil fumarate. The exact mechanism for this is unclear, but may include a drug-drug interaction that inhibits systemic absorption of the antiretroviral drug. HIV RNA levels should be frequently monitored in patients who take XENICAL while being treated for HIV infection. If there is a confirmed increase in HIV viral load, XENICAL should be discontinued.

8 USE IN SPECIFIC POPULATIONS

8.1 Pregnancy

TERATOGENIC EFFECTS

Pregnancy Category X

XENICAL is contraindicated during pregnancy, because weight loss offers no potential benefit to a pregnant woman and may result in fetal harm. A minimum weight gain, and no weight loss, is currently recommended for all pregnant women, including those who are already overweight or obese, due to the obligatory weight gain that occurs in maternal tissues during pregnancy. No embryotoxicity or teratogenicity was seen in animals that received orlistat at doses much higher than the recommended human dose. If this drug is used during pregnancy, or if the patient becomes pregnant while taking this drug, the patient should be apprised of the potential hazard of maternal weight loss to the fetus.

Animal Data

Reproduction studies were conducted in rats and rabbits at doses up to 800 mg/kg/day. Neither study showed embryotoxicity or teratogenicity. This dose is 23 and 47 times the daily human dose calculated on a body surface area (mg/m ^2) basis for rats and rabbits, respectively.

8.3 Nursing Mothers

It is not known if XENICAL is present in human milk. Caution should be exercised when XENICAL is administered to a nursing woman.

8.4 Pediatric Use

Safety and effectiveness in pediatric patients below the age of 12 have not been established.

The safety and efficacy of XENICAL have been evaluated in obese adolescent patients aged 12 to 16 years. Use of XENICAL in this age group is supported by evidence from adequate and well-controlled studies of XENICAL in adults with additional data from a 54-week efficacy and safety study and a 21-day mineral balance study in obese adolescent patients aged 12 to 16 years. Patients treated with XENICAL in the 54-week efficacy and safety study (64.8% female, 75% Caucasians, 18.8% Blacks, and 6.3% Other) had a mean reduction in BMI of 0.55 kg/m ^2 compared with an average increase of 0.31 kg/m ^2 in placebo-treated patients (p=0.001). In both adolescent studies, adverse effects were generally similar to those described in adults and included fatty/oily stool, oily spotting, and oily evacuation. In a subgroup of 152 XENICAL and 77 placebo patients from the 54-week study, changes in body composition measured by DEXA were similar in both treatment groups with the exception of fat mass, which was significantly reduced in patients treated with XENICAL compared to patients treated with placebo (-2.5 kg vs -0.6 kg, p=0.033). Because XENICAL can interfere with the absorption of fat-soluble vitamins, all patients should take a daily multivitamin that contains vitamins A, D, E, K, and beta-carotene. The vitamin supplement should be taken at least 2 hours before or after XENICAL [see Dosage and Administration (2), Warnings and Precautions (5.1), and Clinical Pharmacology (12.3)] .

Plasma concentrations of orlistat and its metabolites M1 and M3 were similar to those found in adults at the same dose level. Daily fecal fat excretions were 27% and 7% of dietary intake in XENICAL and placebo treatment groups, respectively.

8.5 Geriatric Use

Clinical studies of XENICAL did not include sufficient numbers of patients aged 65 years and older to determine whether they respond differently from younger patients [see Clinical Studies (14)] .

9 DRUG ABUSE AND DEPENDENCE

9.2 Abuse

As with any weight-loss agent, the potential exists for abuse of XENICAL in inappropriate patient populations (e.g., patients with anorexia nervosa or bulimia). See Indications and Usage (1) for recommended prescribing guidelines.

10 OVERDOSAGE

Single doses of 800 mg XENICAL and multiple doses of up to 400 mg three times a day for 15 days have been studied in normal weight and obese subjects without significant adverse findings.

Should a significant overdose of XENICAL occur, it is recommended that the patient be observed for 24 hours. Based on human and animal studies, systemic effects attributable to the lipase-inhibiting properties of XENICAL should be rapidly reversible.

11 DESCRIPTION

XENICAL (orlistat) is a gastrointestinal lipase inhibitor for obesity management that acts by inhibiting the absorption of dietary fats.

Orlistat is (S)-2-formylamino-4-methyl-pentanoic acid (S)-1-[[(2S, 3S)-3-hexyl-4-oxo-2-oxetanyl] methyl]-dodecyl ester. Its empirical formula is C 29H 53NO 5, and its molecular weight is 495.7. It is a single diastereomeric molecule that contains four chiral centers, with a negative optical rotation in ethanol at 529 nm. The structure is:

Orlistat is a white to off-white crystalline powder. Orlistat is practically insoluble in water, freely soluble in chloroform, and very soluble in methanol and ethanol. Orlistat has no p Ka within the physiological pH range.

XENICAL is available for oral administration as a turquoise hard-gelatin capsule. The capsule is imprinted with black. Each capsule contains a pellet formulation consisting of 120 mg of the active ingredient, orlistat, as well as the inactive ingredients microcrystalline cellulose, sodium starch glycolate, sodium lauryl sulfate, povidone, and talc. The capsule shell contains gelatin, titanium dioxide, and FD&C Blue No. 2 with black printing ink containing pharmaceutical grade shellac, propylene glycol, strong ammonium solution, potassium hydroxide and black iron oxide.

12 CLINICAL PHARMACOLOGY

12.1 Mechanism of Action

Orlistat is a reversible inhibitor of gastrointestinal lipases. It exerts its therapeutic activity in the lumen of the stomach and small intestine by forming a covalent bond with the active serine residue site of gastric and pancreatic lipases. The inactivated enzymes are thus unavailable to hydrolyze dietary fat in the form of triglycerides into absorbable free fatty acids and monoglycerides. As undigested triglycerides are not absorbed, the resulting caloric deficit may have a positive effect on weight control.

12.2 Pharmacodynamics

Dose-response Relationship

The dose-response relationship for orlistat in human volunteers is shown in Figure 1. The effect is the percentage of ingested fat excreted, referred to as fecal fat excretion percentage. Both individual data (open circles) and the curve predicted for the population with the maximum-effect model (continuous line) are shown in Figure 1.

Figure 1 Dose-Response Relationship for Orlistat in Human Volunteers

At the recommended therapeutic dose of 120 mg three times a day, orlistat inhibits dietary fat absorption by approximately 30%.

Ethanol does not affect orlistat’s effect on preventing the absorption of fat.

Other Short-term Studies

Adults

In several studies of up to 6-weeks duration, the effects of therapeutic doses of XENICAL on gastrointestinal and systemic physiological processes were assessed in normal weight and obese subjects. Postprandial cholecystokinin plasma concentrations were lowered after multiple doses of XENICAL in two studies but not significantly different from placebo in two other experiments. There were no clinically significant changes observed in gallbladder motility, bile composition or lithogenicity, or colonic cell proliferation rate, and no clinically significant reduction of gastric emptying time or gastric acidity. In addition, no effects on plasma triglyceride levels or systemic lipases were observed with the administration of XENICAL in these studies. In a 3-week study of 28 healthy male volunteers, XENICAL (120 mg three times a day) did not significantly affect the balance of calcium, magnesium, phosphorus, zinc, copper, and iron.

Pediatrics

In a 3-week study of 32 obese adolescents aged 12 to 16 years, XENICAL (120 mg three times a day) did not significantly affect the balance of calcium, magnesium, phosphorus, zinc, or copper. The iron balance was decreased by 64.7 µmole/24 hours and 40.4 µmole/24 hours in XENICAL and placebo treatment groups, respectively.

12.3 Pharmacokinetics

Absorption

Systemic exposure to orlistat is minimal. Following oral dosing with 360 mg ^14C-orlistat, plasma radioactivity peaked at approximately 8 hours; plasma concentrations of intact orlistat were near the limits of detection (<5 ng/mL). In therapeutic studies involving monitoring of plasma samples, detection of intact orlistat in plasma was sporadic and concentrations were low (<10 ng/mL or 0.02 µM), without evidence of accumulation, and consistent with minimal absorption.

Distribution

In vitro orlistat was >99% bound to plasma proteins (lipoproteins and albumin were major binding proteins). Orlistat minimally partitioned into erythrocytes.

Metabolism

Based on an oral ^14C-orlistat mass balance study in obese patients, two metabolites, M1 ((the hydrolyzed β-lactone ring product of orlistat) and M3 (sequential metabolite after M1's cleavage of the N-formyl leucine side-chain), accounted for approximately 42% of total radioactivity in plasma. M1 and M3 have an open β-lactone ring and extremely weak lipase inhibitory activity (1000- and 2500-fold less than orlistat, respectively). In view of this low inhibitory activity and the low plasma levels at the therapeutic dose (average of 26 ng/mL and 108 ng/mL for M1 and M3, respectively, 2 to 4 hours after a dose), these metabolites are considered pharmacologically inconsequential. The primary metabolite M1 had a short half-life (approximately 3 hours) whereas the secondary metabolite M3 eliminated at a slower rate (half-life approximately 13.5 hours).

Elimination

Following a single oral dose of 360 mg ^14C-orlistat in both normal weight and obese subjects, fecal excretion of the unabsorbed drug was found to be the major route of elimination. Orlistat and its M1 and M3 metabolites were also subject to biliary excretion. Approximately 97% of the administered radioactivity was excreted in feces; 83% of that was found to be unchanged orlistat. The cumulative renal excretion of total radioactivity was <2% of the given dose of 360 mg ^14C-orlistat. The time to reach complete excretion (fecal plus urinary) was 3 to 5 days. The disposition of orlistat appeared to be similar between normal weight and obese subjects. Based on limited data, the half-life of the absorbed orlistat is in the range of 1 to 2 hours.

Specific Populations

No pharmacokinetic study was conducted for specific populations such as geriatric, different races, and patients with renal and hepatic impairment.

Drug Interactions

Alcohol

In a multiple-dose study in 30 normal-weight subjects, coadministration of XENICAL and 40 grams of alcohol (e.g., approximately 3 glasses of wine) did not result in alteration of alcohol pharmacokinetics, orlistat pharmacodynamics (fecal fat excretion), or systemic exposure to orlistat.

Amiodarone

In a pharmacokinetic study conducted in healthy volunteers who received 120 mg orlistat three times daily for 13 days and a single dose of 120 mg orlistat on the morning of Day 14 co-administered with a single dose of 1200 mg amiodarone on Day 4, a 23 – 27% reduction in the systemic exposure to amiodarone and desethylamiodarone was observed [see Drug Interactions (7.5)] . The effect of commencing orlistat treatment in patients on stable amiodarone therapy has not been studied.

Cyclosporine

In a multiple-dose study, coadministration of 50 mg cyclosporine twice daily with 120 mg XENICAL three times daily decreased cyclosporine AUC and Cmax by 31% and 25%, respectively. In the same study, administration of 50 mg cyclosporine twice daily three hours after the administration of 120 mg XENICAL three times daily decreased cyclosporine AUC and Cmax by 17% and 4%, respectively.

Digoxin

In 12 normal-weight subjects receiving XENICAL 120 mg three times a day for 6 days, XENICAL did not alter the pharmacokinetics of a single dose of digoxin.

Fat-soluble Vitamin Supplements and Analogues

A pharmacokinetic interaction study showed a 30% reduction in beta-carotene supplement absorption when concomitantly administered with XENICAL. XENICAL inhibited absorption of a vitamin E acetate supplement by approximately 60%. The effect of XENICAL on the absorption of supplemental vitamin D, vitamin A, and nutritionally-derived vitamin K is not known at this time.

Glyburide

In 12 normal-weight subjects receiving orlistat 80 mg three times a day for 5 days, orlistat did not alter the pharmacokinetics or pharmacodynamics (blood glucose-lowering) of glyburide.

Nifedipine (extended-release tablets)

In 17 normal-weight subjects receiving XENICAL 120 mg three times a day for 6 days, XENICAL did not alter the bioavailability of nifedipine (extended-release tablets).

Oral Contraceptives

In 20 normal-weight female subjects, the treatment of XENICAL 120 mg three times a day for 23 days resulted in no changes in the ovulation-suppressing action of oral contraceptives.

Phenytoin

In 12 normal-weight subjects receiving XENICAL 120 mg three times a day for 7 days, XENICAL did not alter the pharmacokinetics of a single 300-mg dose of phenytoin.

Pravastatin

In a 2-way crossover study of 24 normal-weight, mildly hypercholesterolemic patients receiving XENICAL 120 mg three times a day for 6 days, XENICAL did not affect the pharmacokinetics of pravastatin.

Warfarin

In 12 normal-weight subjects, administration of XENICAL 120 mg three times a day for 16 days did not result in any change in either warfarin pharmacokinetics (both R- and S-enantiomers) or pharmacodynamics (prothrombin time and serum Factor VII). Although undercarboxylated osteocalcin, a marker of vitamin K nutritional status, was unaltered with XENICAL administration, vitamin K levels tended to decline in subjects taking XENICAL. Therefore, as vitamin K absorption may be decreased with XENICAL, patients on chronic stable doses of warfarin who are prescribed XENICAL should be monitored closely for changes in coagulation parameters.

13 NONCLINICAL TOXICOLOGY

13.1 Carcinogenesis, Mutagenesis, Impairment of Fertility

Carcinogenicity studies in rats and mice did not show a carcinogenic potential for orlistat at doses up to 1000 mg/kg/day and 1500 mg/kg/day, respectively. For mice and rats, these doses are 38 and 46 times the daily human dose calculated on an area under concentration vs time curve basis of total drug-related material.

Orlistat had no detectable mutagenic or genotoxic activity as determined by the Ames test, a mammalian forward mutation assay (V79/HPRT), an in vitro clastogenesis assay in peripheral human lymphocytes, an unscheduled DNA synthesis assay (UDS) in rat hepatocytes in culture, and an in vivo mouse micronucleus test.

When given to rats at a dose of 400 mg/kg/day in a fertility and reproduction study, orlistat had no observable adverse effects. This dose is 12 times the daily human dose calculated on a body surface area (mg/m^2) basis.

14 CLINICAL STUDIES

The long-term effects of XENICAL on morbidity and mortality associated with obesity have not been established.

The effects of XENICAL on weight loss, weight maintenance, and weight regain and on a number of comorbidities (e.g., type 2 diabetes, lipids, blood pressure) were assessed in the 4-year XENDOS study and in seven long-term (1- to 2-years duration) multicenter, double-blind, placebo-controlled clinical trials. During the first year of therapy, the studies of 2-year duration assessed weight loss and weight maintenance. During the second year of therapy, some studies assessed continued weight loss and weight maintenance and others assessed the effect of XENICAL on weight regain. These studies included over 2800 patients treated with XENICAL and 1400 patients treated with placebo (age range 17-78 years, 80.2% women, 91.0% Caucasians, 5.7% Blacks, 2.3% Hispanics, 0.9% Other). The majority of these patients had obesity-related risk factors and comorbidities. In the XENDOS study, which included 3304 patients (age range 30-58 years, 55% women, 99% Caucasians, 1% other), the time to onset of type 2 diabetes was assessed in addition to weight management. In all these studies, treatment with XENICAL and placebo designates treatment with XENICAL plus diet and placebo plus diet, respectively.

During the weight loss and weight maintenance period, a well-balanced, reduced-calorie diet that was intended to result in an approximate 20% decrease in caloric intake and provide 30% of calories from fat was recommended to all patients. In addition, all patients were offered nutritional counseling.

14.1 One-year Results: Weight Loss, Weight Maintenance, and Risk Factors

Pooled data from five clinical trials indicated that the overall mean weight loss from randomization to the end of 1 year of treatment in the intent-to-treat population was 13.4 lbs in the patients treated with XENICAL and 5.8 lbs in the placebo-treated patients. After 1 year of treatment, the mean percent weight loss difference between XENICAL-treated patients and placebo-treated patients was 3%. One thousand seventy two (69%) patients treated with XENICAL and 701 (63%) patients treated with placebo completed 1 year of treatment. Of the patients who completed 1 year of treatment, 57% of the patients treated with XENICAL (120 mg three times a day) and 31% of the placebo-treated patients lost at least 5% of their baseline body weight.

The percentages of patients achieving ≥5% and ≥10% weight loss after 1 year in five large multicenter studies for the intent-to-treat populations are presented in Table 6.

Table 6 Percentage of Patients Losing ≥5% and ≥10% of Body Weight From Randomization After 1-Year Treatment [Treatment designates XENICAL 120 mg three times a day plus diet or placebo plus diet]
Study No. | Intent-to-Treat Population [Last observation carried forward]
Study No. | ≥5% Weight Loss |  |  |  |  | ≥10% Weight Loss
Study No. | XENICAL | n | Placebo | n | p-value | XENICAL | n | Placebo | n | p-value
14119B | 35.5% | 110 | 21.3% | 108 | 0.021 | 16.4% | 110 | 6.5% | 108 | 0.022
14119C | 54.8% | 343 | 27.4% | 340 | <0.001 | 24.8% | 343 | 8.2% | 340 | <0.001
14149 | 50.6% | 241 | 26.3% | 236 | <0.001 | 22.8% | 241 | 11.9% | 236 | 0.02
14161 [All studies, with the exception of 14161, were conducted at centers specialized in treating obesity and complications of obesity. Study 14161 was conducted with primary care physicians.] | 37.1% | 210 | 16.0% | 212 | <0.001 | 19.5% | 210 | 3.8% | 212 | <0.001
14185 | 42.6% | 657 | 22.4% | 223 | <0.001 | 17.7% | 657 | 9.9% | 223 | 0.006
The diet utilized during year 1 was a reduced-calorie diet.

The relative changes in risk factors associated with obesity following 1 year of therapy with XENICAL and placebo are presented for the population as a whole and for the population with abnormal values at randomization.

Population as a Whole

The changes in metabolic, cardiovascular and anthropometric risk factors associated with obesity based on pooled data for five clinical studies, regardless of the patient's risk factor status at randomization, are presented in Table 7. One year of therapy with XENICAL resulted in relative improvement in several risk factors.

Table 7 Mean Change in Risk Factors From Randomization Following 1-Year Treatment [Treatment designates XENICAL 120 mg three times a day plus diet or placebo plus diet] Population as a Whole
Risk Factor | XENICAL 120 mg [Intent-to-treat population at week 52, observed data based on pooled data from 5 studies] | Placebo
Metabolic:
Total Cholesterol | -2.0% | +5.0%
LDL-Cholesterol | -4.0% | +5.0%
HDL-Cholesterol | +9.3% | +12.8%
LDL/HDL | -0.37 | -0.20
Triglycerides | +1.34% | +2.9%
Fasting Glucose, mmol/L | -0.04 | +0.0
Fasting Insulin, pmol/L | -6.7 | +5.2
Cardiovascular:
Systolic Blood Pressure, mm Hg | -1.01 | +0.58
Diastolic Blood Pressure, mm Hg | -1.19 | +0.46
Anthropometric:
Waist Circumference, cm | -6.45 | -4.04
Hip Circumference, cm | -5.31 | -2.96

Population With Abnormal Risk Factors at Randomization

The changes from randomization following 1-year treatment in the population with abnormal lipid levels (LDL ≥130 mg/dL, LDL/HDL ≥3.5, HDL <35 mg/dL) were greater for XENICAL compared to placebo with respect to LDL-cholesterol (-7.83% vs +1.14%) and the LDL/HDL ratio (-0.64 vs -0.46). HDL increased in the placebo group by 20.1% and in the XENICAL group by 18.8%. In the population with abnormal blood pressure at baseline (systolic BP ≥140 mm Hg), the change in SBP from randomization to 1 year was greater for XENICAL (-10.89 mm Hg) than placebo (-5.07 mm Hg). For patients with a diastolic blood pressure ≥90 mm Hg, XENICAL patients decreased by -7.9 mm Hg while the placebo patients decreased by -5.5 mm Hg. Fasting insulin decreased more for XENICAL than placebo (-39 vs -16 pmol/L) from randomization to 1 year in the population with abnormal baseline values (≥120 pmol/L). A greater reduction in waist circumference for XENICAL vs placebo (-7.29 vs -4.53 cm) was observed in the population with abnormal baseline values (≥100 cm).

14.2 Effect on Weight Regain

Three studies were designed to evaluate the effects of XENICAL compared to placebo in reducing weight regain after a previous weight loss achieved following either diet alone (one study, 14302) or prior treatment with XENICAL (two studies, 14119C and 14185). The diet utilized during the 1-year weight regain portion of the studies was a weight-maintenance diet, rather than a weight-loss diet, and patients received less nutritional counseling than patients in weight-loss studies. For studies 14119C and 14185, patients' previous weight loss was due to 1 year of treatment with XENICAL in conjunction with a mildly hypocaloric diet. Study 14302 was conducted to evaluate the effects of 1 year of treatment with XENICAL on weight regain in patients who had lost 8% or more of their body weight in the previous 6 months on diet alone.

In study 14119C, patients treated with placebo regained 52% of the weight they had previously lost while the patients treated with XENICAL regained 26% of the weight they had previously lost (p<0.001). In study 14185, patients treated with placebo regained 63% of the weight they had previously lost while the patients treated with XENICAL regained 35% of the weight they had lost (p<0.001). In study 14302, patients treated with placebo regained 53% of the weight they had previously lost while the patients treated with XENICAL regained 32% of the weight that they had lost (p<0.001).

14.3 Two-year Results: Long-term Weight Control and Risk Factors

The treatment effects of XENICAL were examined for 2 years in four of the five 1-year weight management clinical studies previously discussed (see Table 6). At the end of year 1, the patients' diets were reviewed and changed where necessary. The diet prescribed in the second year was designed to maintain patient's current weight. XENICAL was shown to be more effective than placebo in long-term weight control in four large, multicenter, 2-year double-blind, placebo-controlled studies.

Pooled data from four clinical studies indicate that 74% of all patients treated with 120 mg three times a day of XENICAL and 76% of patients treated with placebo completed 2 years of the same therapy. Pooled data from four clinical studies indicate that the mean weight loss difference between XENICAL 120 mg three times a day and placebo treatment groups at year 2 in those patients who completed 1 year of treatment (ITT LOCF) was 3%. In the same studies cited in the One-year Results (see Table 6), the percentages of patients achieving a ≥5% and ≥10% weight loss after 2 years are shown in Table 8.

Table 8 Percentage of Patients Losing ≥5% and ≥10% of Body Weight From Randomization After 2-Year Treatment [Treatment designates XENICAL 120 mg three times a day plus diet or placebo plus diet]
Study No. | Intent-to-Treat Population [Last observation carried forward]
Study No. | ≥5% Weight Loss |  |  |  |  | ≥10% Weight Loss
Study No. | XENICAL | n | Placebo | n | p-value | XENICAL | n | Placebo | n | p-value
14119C | 45.1% | 133 | 23.6% | 123 | <0.001 | 24.8% | 133 | 6.5% | 123 | <0.001
14149 | 43.3% | 178 | 27.2% | 158 | 0.002 | 18.0% | 178 | 9.5% | 158 | 0.025
14161 [All studies, with the exception of 14161, were conducted at centers specializing in treating obesity or complications of obesity. Study 14161 was conducted with primary care physicians.] | 25.0% | 148 | 15.0% | 113 | 0.049 | 16.9% | 148 | 3.5% | 113 | 0.001
14185 | 34.0% | 147 | 27.9% | 122 | 0.279 | 17.7% | 147 | 11.5% | 122 | 0.154
The diet utilized during year 2 was designed for weight maintenance and not weight loss.

The relative changes in risk factors associated with obesity following 2 years of therapy were also assessed in the population as a whole and the population with abnormal risk factors at randomization.

Population as a Whole

The relative differences in risk factors between treatment with XENICAL and placebo were similar to the results following 1 year of therapy for total cholesterol, LDL-cholesterol, LDL/HDL ratio, triglycerides, fasting glucose, fasting insulin, diastolic blood pressure, waist circumference, and hip circumference. The relative differences between treatment groups for HDL cholesterol and systolic blood pressure were less than that observed in the year one results.

Population With Abnormal Risk Factors at Randomization

The relative differences in risk factors between treatment with XENICAL and placebo were similar to the results following 1 year of therapy for LDL- and HDL-cholesterol, triglycerides, fasting insulin, diastolic blood pressure, and waist circumference. The relative differences between treatment groups for LDL/HDL ratio and isolated systolic blood pressure were less than that observed in the year one results.

14.4 Four-year Results: Long-term Weight Control and Risk Factors

In the 4-year double-blind, placebo-controlled XENDOS study, the effects of XENICAL in delaying the onset of type 2 diabetes and on body weight were compared to placebo in 3304 obese patients who had either normal or impaired glucose tolerance at baseline. Thirty-four percent of the 1655 patients who were randomized to the placebo group and 52% of the 1649 patients who were randomized to the XENICAL group completed the 4-year study.

At the end of the study, the mean percent weight loss in the placebo group was -2.75% compared with -5.17% in the XENICAL group (p<0.001) (see Figure 2). Forty-five percent of the placebo patients and 73% of the XENICAL patients lost ≥5% of their baseline body weight, and 21% of the placebo patients and 41% of the XENICAL patients lost ≥10% of their baseline body weight following the first year of treatment. Following 4 years of treatment, 28% of the placebo patients and 45% of the XENICAL patients lost ≥5% of their baseline body weight and 10% of the placebo patients and 21% of the XENICAL patients lost ≥10% of their baseline body weight. After 4 years of treatment, the mean % difference in weight loss between XENICAL treated patients and placebo was 2.5%.

Figure 2 Mean Change from Baseline Body Weight (Kgs) Over Time*

*ITT LOCF study population

The relative changes from baseline in risk factors associated with obesity following 4 years of therapy were assessed in the XENDOS study population (see Table 9).

Table 9 Mean Change in Risk Factors From Randomization Following 4-Years Treatment [Treatment designates XENICAL 120 mg three times a day plus diet or placebo plus diet]
Risk Factor | XENICAL 120 mg [Intent-to-treat population] | Placebo
Metabolic:
Total Cholesterol | -7.02% | -2.03%
LDL-Cholesterol | -11.66% | -3.85%
HDL-Cholesterol | +5.92% | +7.01%
LDL/HDL | -0.53 | -0.33
Triglycerides | +3.64% | +1.30
Fasting Glucose, mmol/L | +0.12 | +0.23
Fasting Insulin, pmol/L | -24.93 | -15.71
Cardiovascular:
Systolic Blood Pressure, mm Hg | -4.12 | -2.60
Diastolic Blood Pressure, mm Hg | -1.93 | -0.87
Anthropometric:
Waist Circumference, cm | -5.78 | -3.99

Onset of Type 2 Diabetes in Obese Patients

In the XENDOS trial, in the overall population, XENICAL delayed the onset of type 2 diabetes such that at the end of four years of treatment the cumulative incidence rate of diabetes was 8.3% for the placebo group compared to 5.5% for the XENICAL group, p=0.01 (see Table 10). This finding was driven by a statistically-significant reduction in the incidence of developing type 2 diabetes in those patients who had impaired glucose tolerance at baseline (Table 10 and Figure 3). XENICAL did not reduce the risk for the development of diabetes in patients with normal glucose tolerance at baseline.

The effect of XENICAL to delay the onset of type 2 diabetes in obese patients with IGT is presumably due to weight loss, and not to any independent effects of the drug on glucose or insulin metabolism. The effect of XENICAL on weight loss is adjunctive to diet and exercise.

Table 10 Incidence Rate of Diabetes at Year 4 by OGTT Status at Baseline [Based on patients with a baseline and at least one follow-up OGTT measurement, ITT LOCF study population.]
OGTT at Baseline | Normal |  | Impaired |  | All
Treatment | Placebo | XENICAL | Placebo | XENICAL | Placebo | XENICAL
Number of patients | 1148 | 1235 | 324 | 337 | 1472 | 1572
# pts developing diabetes | 16 | 21 | 62 | 48 | 78 | 69
Life table rate [Rate adjusted for dropouts] | 2.1% | 1.7% | 27.2% | 18.7% | 8.3% | 5.5%
Observed percent | 1.4% | 1.7% | 19.1% | 14.2% | 5.3% | 4.4%
Absolute risk reduction
Life table | 0.4% |  | 8.5% |  | 2.8%
Observed | -0.3% |  | 4.9% |  | 0.9%
Relative risk reduction [Computed as (1- hazard ratio)] | 8% |  | 42% |  | 34%
p-value | 0.79 |  | <0.01 |  | 0.01

Figure 3 Percentage of Patients Without Diabetes Over Time

14.5 Study of Patients With Type 2 Diabetes

A 1-year double-blind, placebo-controlled study in type 2 diabetics (N=321) stabilized on sulfonylureas was conducted. Thirty percent of patients treated with XENICAL achieved at least a 5% or greater reduction in body weight from randomization compared to 13% of the placebo-treated patients (p<0.001). Table 11 describes the changes over 1 year of treatment with XENICAL compared to placebo, in sulfonylurea usage and dose reduction as well as in hemoglobin HbA1c, fasting glucose, and insulin.

Table 11 Mean Changes in Body Weight and Glycemic Control From Randomization Following 1-Year Treatment in Patients With Type 2 Diabetes
 | XENICAL 120 mg [Treatment designates XENICAL 120 mg three times a day plus diet or placebo plus diet] (n=162) | Placebo (n=159) | Statistical Significance
% patients who discontinued dose of oral sulfonylurea | 11.7% | 7.5% | [Statistically significant (p≤0.05) based on intent-to-treat, last observation carried forward ns nonsignificant, p>0.05]
% patients who decreased dose of oral sulfonylurea | 31.5% | 21.4%
Average reduction in sulfonylurea medication dose | -22.8% | -9.1%
Body weight change (lbs) | -8.9 | -4.2
HbA1c | -0.18% | +0.28%
Fasting glucose, mmol/L | -0.02 | +0.54
Fasting insulin, pmol/L | -19.68 | -18.02 | ns
Statistical significance based on intent-to-treat population, last observation carried forward.

In addition, XENICAL (n=162) compared to placebo (n=159) was associated with significant lowering for total cholesterol (-1.0% vs +9.0%, p≤0.05), LDL-cholesterol (-3.0% vs +10.0%, p≤0.05), LDL/HDL ratio (-0.26 vs -0.02, p≤0.05) and triglycerides (+2.54% vs +16.2%, p≤0.05), respectively. For HDL cholesterol, there was a +6.49% increase on XENICAL and +8.6% increase on placebo, p>0.05. Systolic blood pressure increased by +0.61 mm Hg on XENICAL and increased by +4.33 mm Hg on placebo, p>0.05. Diastolic blood pressure decreased by -0.47 mm Hg for XENICAL and by -0.5 mm Hg for placebo, p>0.05.

14.6 Glucose Tolerance in Obese Patients

Two-year studies that included oral glucose tolerance tests were conducted in obese patients not previously diagnosed or treated for type 2 diabetes and whose baseline oral glucose tolerance test (OGTT) status at randomization was either normal, impaired, or diabetic.

The progression from a normal OGTT at randomization to a diabetic or impaired OGTT following 2 years of treatment with XENICAL (n=251) or placebo (n=207) were compared. Following treatment with XENICAL, 0.0% and 7.2% of the patients progressed from normal to diabetic and normal to impaired, respectively, compared to 1.9% and 12.6% of the placebo treatment group, respectively.

In patients found to have an impaired OGTT at randomization, the percent of patients improving to normal or deteriorating to diabetic status following 1 and 2 years of treatment with XENICAL compared to placebo are presented. After 1 year of treatment, 45.8% of the placebo patients and 73% of the XENICAL patients had a normal oral glucose tolerance test while 10.4% of the placebo patients and 2.6% of the XENICAL patients became diabetic. After 2 years of treatment, 50% of the placebo patients and 71.7% of the XENICAL patients had a normal oral glucose tolerance test while 7.5% of placebo patients were found to be diabetic and 1.7% of XENICAL patients were found to be diabetic after treatment.

14.7 Pediatric Clinical Studies

The effects of XENICAL on body mass index (BMI) and weight loss were assessed in a 54-week multicenter, double-blind, placebo-controlled study in 539 obese adolescents (357 receiving XENICAL 120 mg three times a day, 182 receiving placebo), aged 12 to 16 years. All study participants had a baseline BMI that was 2 units greater than the US weighted mean for the 95th percentile based on age and gender. Body mass index was the primary efficacy parameter because it takes into account changes in height and body weight, which occur in growing children.

During the study, all patients were instructed to take a multivitamin containing fat-soluble vitamins at least 2 hours before or after ingestion of XENICAL. Patients were also maintained on a well-balanced, reduced-calorie diet that was intended to provide 30% of calories from fat. In addition, all patients were placed on a behavior modification program and offered exercise counseling.

Approximately 65% of patients in each treatment group completed the study.

Following one year of treatment, BMI decreased by an average of 0.55 kg/m^2 in the XENICAL-treated patients and increased by an average of 0.31 kg/m^2 in the placebo-treated patients (p=0.001).

The percentages of patients achieving ≥5% and ≥10% reduction in BMI and body weight after 52 weeks of treatment for the intent-to-treat population are presented in Table 12.

Table 12 Percentages of Patients with ≥5% and ≥10% Decrease in Body Mass Index and Body Weight After 1-Year Treatment [Treatment designates XENICAL 120 mg three times a day plus diet or placebo plus diet] (Protocol NM16189)
 | Intent-to-Treat Population [Last observation carried forward]
 | ≥5% Decrease |  |  |  | ≥10% Decrease
 | XENICAL | n | Placebo | n | XENICAL | n | Placebo | n
BMI | 26.5% | 347 | 15.7% | 178 | 13.3% | 347 | 4.5% | 178
Body Weight | 19.0% | 348 | 11.7% | 180 | 9.5% | 348 | 3.3% | 180

16 HOW SUPPLIED/STORAGE AND HANDLING

XENICAL is a turquoise, hard-gelatin capsule containing pellets of powder.

XENICAL 120 mg Capsules: Turquoise, two-piece, No. 1 opaque hard-gelatin capsule imprinted with XENICAL 120 in black ink — bottle of 90 (NDC 61269-460-90).

Storage and Handling

Store at 25°C (77°F); excursions permitted to 15° to 30°C (59° to 86°F) [see USP Controlled Room Temperature]. Keep bottle tightly closed.

XENICAL should not be used after the given expiration date.

17 PATIENT COUNSELING INFORMATION

See FDA-approved patient labeling (Patient Information).

Information for Patients

Patients should not take XENICAL if they are pregnant, have chronic malabsorption syndrome, cholestasis or hypersensitivity to XENICAL or to any component of this product [see Contraindications (4)] .

Concomitant Medications

Patients should be asked if they are taking cyclosporine, beta carotene or vitamin E supplements, levothyroxine, warfarin, antiepileptic drugs, amiodarone, or antiretroviral drugs due to potential interactions [see Drug Interactions (7)] .

Commonly Observed Adverse Events

Patients should be informed of the commonly-observed adverse events associated with the use of XENICAL which include oily spotting, flatus with discharge, fecal urgency, fatty/oily stool, oily evacuation, increased defecation, fecal incontinence [see Adverse Reactions (6.1)] .

Potential Risks and Benefits

Patients should be informed of potential risks which include lowered absorption of fat-soluble vitamins and potential liver injury, increases in urinary oxalate, and cholelithiasis [see Warnings and Precautions (5)] . Treatment with XENICAL may result in weight loss and improvement in obesity-related risk factors due to weight loss [see Clinical Studies (14)] .

Dosing Instructions

Patients should be counseled to take XENICAL as directed with meals or up to one hour after a meal. Patients should also be advised to take multivitamin supplementation at least two hours before or after the administration of XENICAL, or at bedtime [see Dosage and Administration (2)] .

XENICAL® is a registered trademark of CHEPLAPHARM Arzneimittel GmbH.

Licensed by:
CHEPLAPHARM Arzneimittel GmbH
Ziegelhof 24
17489 Greifswald, Germany

Distributed by:
H2-Pharma, LLC
611 Industrial Park Blvd
Montgomery, AL 36117, USA

© 2022 CHEPLAPHARM Arzneimittel GmbH. All rights reserved.

Patient Information
XENICAL® (zen´i-cal)
(orlistat)
Capsules

Read this Patient Information before you start taking XENICAL and each time you get a refill. There may be new information. This information does not take the place of talking to your doctor about your medical condition or your treatment.

What is XENICAL?

XENICAL is a prescription medicine used with a low calorie diet to increase weight loss in people with obesity. XENICAL may help obese people lose weight and keep the weight off.

It is not known if XENICAL is safe and effective in children under 12 years old.

Who should not take XENICAL?

Do not take XENICAL if you:

- are pregnant. A minimum weight gain, and no weight loss, is currently recommended for all pregnant women, including those who are already overweight or obese.
- always have problems absorbing food (chronic malabsorption)
- have gallbladder problems (cholestasis)
- are allergic to orlistat or any of the ingredients in XENICAL. See the end of this leaflet for a complete list of ingredients in XENICAL

Before you take XENICAL, tell your doctor about all of your medical conditions, including if you

- have liver problems
- have kidney problems
- have problems with your thyroid
- have eating problems such as anorexia or bulimia
- have diabetes
- have a seizure disorder (epilepsy)
- have an abnormal heart rhythm (arrhythmia)
- have the human immunodeficiency virus (HIV)
- are breastfeeding or plan to breastfeed. It is not known if XENICAL passes into your breast milk. Talk to your doctor before you breastfeed and take XENICAL.
- are pregnant or plan to become pregnant. Do not take XENICAL if you are pregnant or plan to become pregnant.

Tell your doctor about all the medicines you take, including prescription and over-the-counter medicines, vitamins, and herbal supplements.

XENICAL and other medicines may affect each other causing side effects. XENICAL may affect the way other medicines work, and other medicines may affect the way XENICAL works.

Especially tell your doctor if you are taking:

- cyclosporine (Gengraf, Neoral, Sandimmune, Restasis, Sangcya)
- beta-carotene or vitamin E supplements
- levothyroxine (Levo-T, Levolet, Levothyroid, Levothyroxine Sodium, Levoxyl, Novothyrox, Synthroid, Tirosint, Unithroid).
- warfarin (Athrombin, Athrombin-K, Coumadin, Jantoven, Panwarfin, Warfarin Sodium)
- amiodarone (Cordarone, Pacerone)
- medicines used to treat seizures. They may not work as well while you take XENICAL. Talk to your doctor right away if your seizures happen more often or get worse while you take XENICAL.
- antiretroviral medicines used to treat HIV. They may not work as well while you take XENICAL.

Know the medicines you take. Keep a list of your medicines and show it to your doctor and pharmacist when you get a new medicine.

How should I take XENICAL?

- Take XENICAL exactly as your doctor tells you to take it.
- Your doctor will tell you how much XENICAL to take and when to take it.
- Take XENICAL with your meals or up to one hour after your meal. If you miss a meal or have a meal without fat, you can skip your dose of XENICAL. If you take a cyclosporine medicine, take XENICAL and cyclosporine at least 3 hours apart. See " What should I tell my doctor before taking XENICAL?" for a complete list of cyclosporine medicines.
- If you take a multivitamin, take it at least 2 hours before or after you take XENICAL. Bedtime is a good time to take your multivitamin.
- If you take a levothyroxine medicine, take XENICAL and levothyroxine at least 4 hours apart. See " What should I tell my doctor before taking XENICAL?" for a complete list of levothyroxine medicines.
- Take XENICAL with a nutritionally balanced, low calorie diet that has no more than about 30% of calories from fat. Taking XENICAL with any meal high in fat (more than 30% fat) may make the common side effects worse. See Table 1.

Table 1
IF YOUR DAILY CALORIE LEVEL IS: | THE RECOMMENDED DAILY GRAMS OF FAT (in a 30% fat diet) ARE:
1500 | 50
1600 | 53
1800 | 60
2000 | 67

- If you take too much XENICAL call your doctor or go to the nearest hospital emergency room right away.

What are the possible risks of XENICAL?

XENICAL may cause serious side effects, including:

- Lowered absorption of certain vitamins in your body. Take a multivitamin containing vitamins A, D, E, K, and beta-carotene one time each day. Take a multivitamin at least 2 hours before or after you take XENICAL, such as at bedtime.
- Severe liver problems.Stop taking XENICAL and call your doctor right away if you have the following symptoms of liver problems:
  - loss of appetite
  - itchy skin
  - yellowing of your skin or the white part of your eyes
  - amber-colored urine
  - light-colored bowel movements (stools)
  - pain in the upper right portion of your stomach
- Kidney problems.Your doctor may do certain tests to check your kidney function during treatment with XENICAL. Call your doctor right away if you have the following symptoms of kidney problems:
  - swelling, especially of the legs and feet
  - little or no urine output
  - frequent or painful urination
  - blood in the urine
  - loss of appetite, nausea and vomiting
  - severe pain in the back, belly or groin
- Gallbladder problems (gallstones).Call your doctor right away if you have the following symptoms of gallstones:
  - pain in the upper right portion of your stomach
  - nausea
  - vomiting

The most common side effects of XENICAL include:

- oily [Oily discharge may be clear or have an orange or brown color.] rectal discharge
- passing gas with oily discharge
- urgent need to have a bowel movement
- oily or fatty stools
- increased number of bowel movements
- being unable to control your bowel movements

These are not all the possible side effects of XENICAL.

Call your doctor for medical advice about side effects. You may report side effects to FDA at 1-800-FDA-1088.

How should I store XENICAL?

- Store XENICAL at 59°F to 86°F (15°C to 30°C).
- Keep XENICAL in a tightly closed container.
- Do not use XENICAL after the expiration date on the bottle.
- Safely throw away medicine that is out of date or no longer needed.

Keep XENICAL and all medicines out of the reach of children.

General information about the safe and effective use of XENICAL.

Medicines are sometimes prescribed for purposes other than those listed in a Patient Information leaflet. Do not use XENICAL for a condition for which it was not prescribed. Do not give XENICAL to other people, even if they have the same symptoms that you have. It may harm them.

This Patient Information leaflet summarizes the most important information about XENICAL. If you would like more information, talk with your doctor. You can ask your pharmacist or doctor for information about XENICAL that is written for health professionals.

For more information, call the Safety Call Center at 1-888-236-5445.

What are the ingredients in XENICAL?

Active Ingredient: orlistat

Inactive Ingredients: microcrystalline cellulose, sodium starch glycolate, sodium lauryl sulfate, povidone, talc, gelatin and titanium dioxide.

Turquoise capsule shell: FD&C Blue No. 2, with black printing ink containing pharmaceutical grade shellac, propylene glycol, strong ammonium solution, potassium hydroxide and black iron oxide.

Other Information: Body Mass Index

The chart below illustrates body mass index (BMI) according to a variety of weights and heights. XENICAL is intended for patients with a BMI of greater than or equal to 30 kg/m ^2 or a BMI of greater than or equal to 27 kg/m ^2 in the presence of other risk factors such as hypertension, diabetes, or high cholesterol. The BMI is calculated by dividing your weight in kilograms by your height in meters squared. To use this chart:

- Find the height closest to your height in the left-hand column.
- Then move across the top row to find the weight closest to your weight.
- The number where these two meet is your BMI. (For example, a person who weighs 180 lbs and is 5'5" has a BMI of 30.)

This Patient Information has been approved by the U.S. Food and Drug Administration.

XENICAL® is a registered trademark of CHEPLAPHARM Arzneimittel GmbH.

Licensed by:
CHEPLAPHARM Arzneimittel GmbH
Ziegelhof 24, 17489 Greifswald, Germany

Distributed by:
H2-Pharma, LLC
611 Industrial Park Blvd, Montgomery, AL 36117, USA

PPI Revised: 11/2022
© 2022 CHEPLAPHARM Arzneimittel GmbH.
All rights reserved.

Representative sample of labeling (see the HOW SUPPLIED section for complete listing):

PRINCIPAL DISPLAY PANEL - 120 mg Capsule Bottle Label

NDC 61269-460-90

Xenical®
(orlistat)

120 mg

Each capsule contains
120 mg orlistat.

Rx only

90 capsules

CHEPLAPHARM Arzneimittel